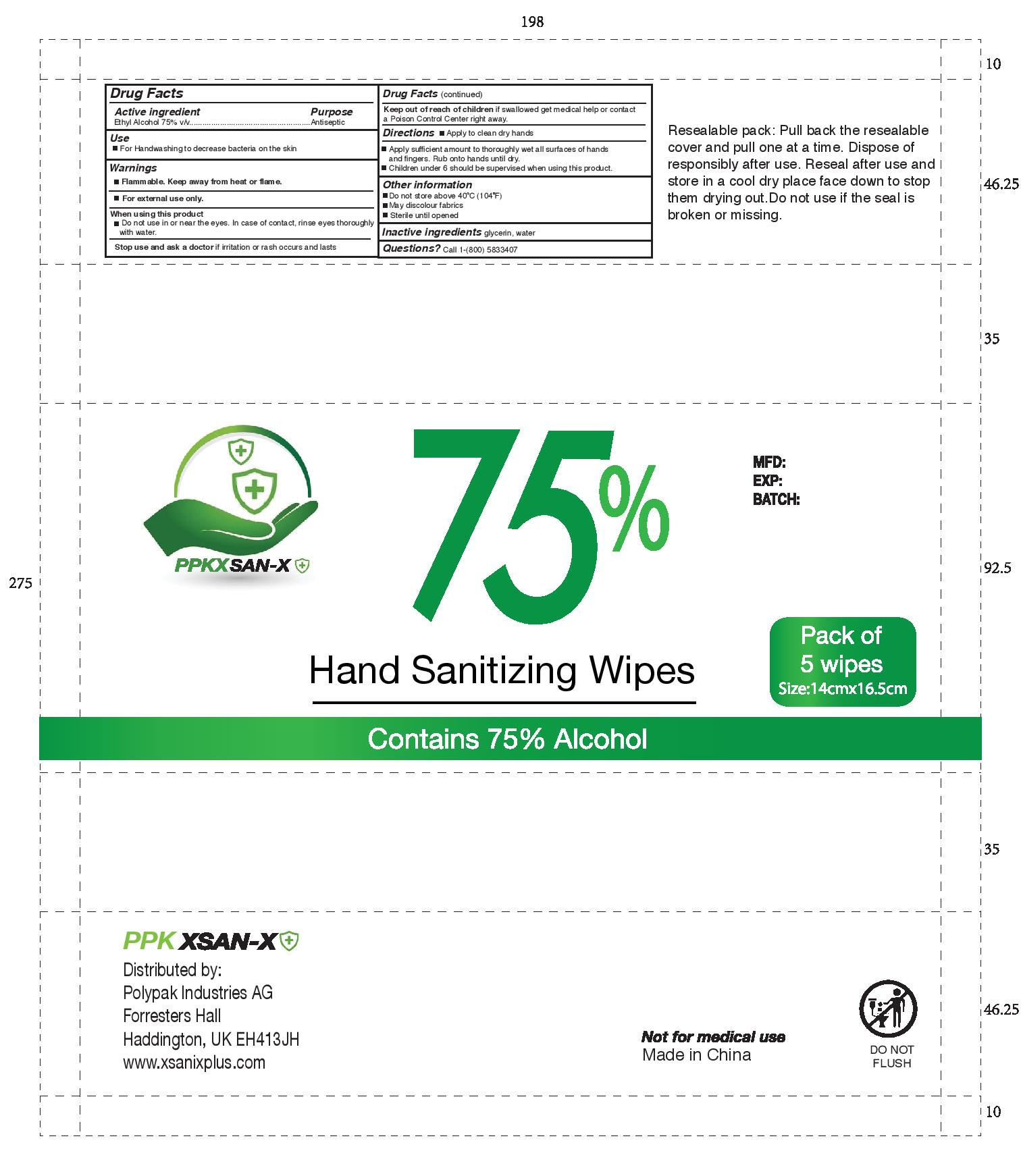 DRUG LABEL: Hand Sanitizer Wipes
NDC: 80285-129 | Form: CLOTH
Manufacturer: Polypak Industries AG
Category: otc | Type: HUMAN OTC DRUG LABEL
Date: 20201029

ACTIVE INGREDIENTS: ALCOHOL 75 mL/100 mL
INACTIVE INGREDIENTS: GLYCERIN; WATER

DOSAGE AND ADMINISTRATION

For Handwashing to decrease bacteria on the skin

Apply sufficient amount to thoroughly wet all surfaces of hands
and fingers. Rub onto hands until dry.
Children under 6 should be supervised when using this product.

WARNINGS

Flammable. Keep away from heat or flame.
When using this product
Do not use in or near the eyes. In case of contact, rinse eyes thoroughly
with water.
Keep out of reach of children if swallowed get medical help or contact
a Poison Control Center right away.
Stop use and ask a doctor if irritation or rash occurs and lasts

INACTIVE INGREDIENT

glycerin, water

INDICATIONS AND USAGE

For Handwashing to decrease bacteria on the skin

Keep out of reach of children if swallowed get medical help or contact a Poison Control Center right away.

PURPOSE

Hand sanitizing wipes - for handwashing to decrease bacteria on the skin

ACTIVE INGREDIENT

Alcohol - 75%

PACKAGE LABEL

alcoholwipepolypak.jpg

alcoholwipepolypak.jpg